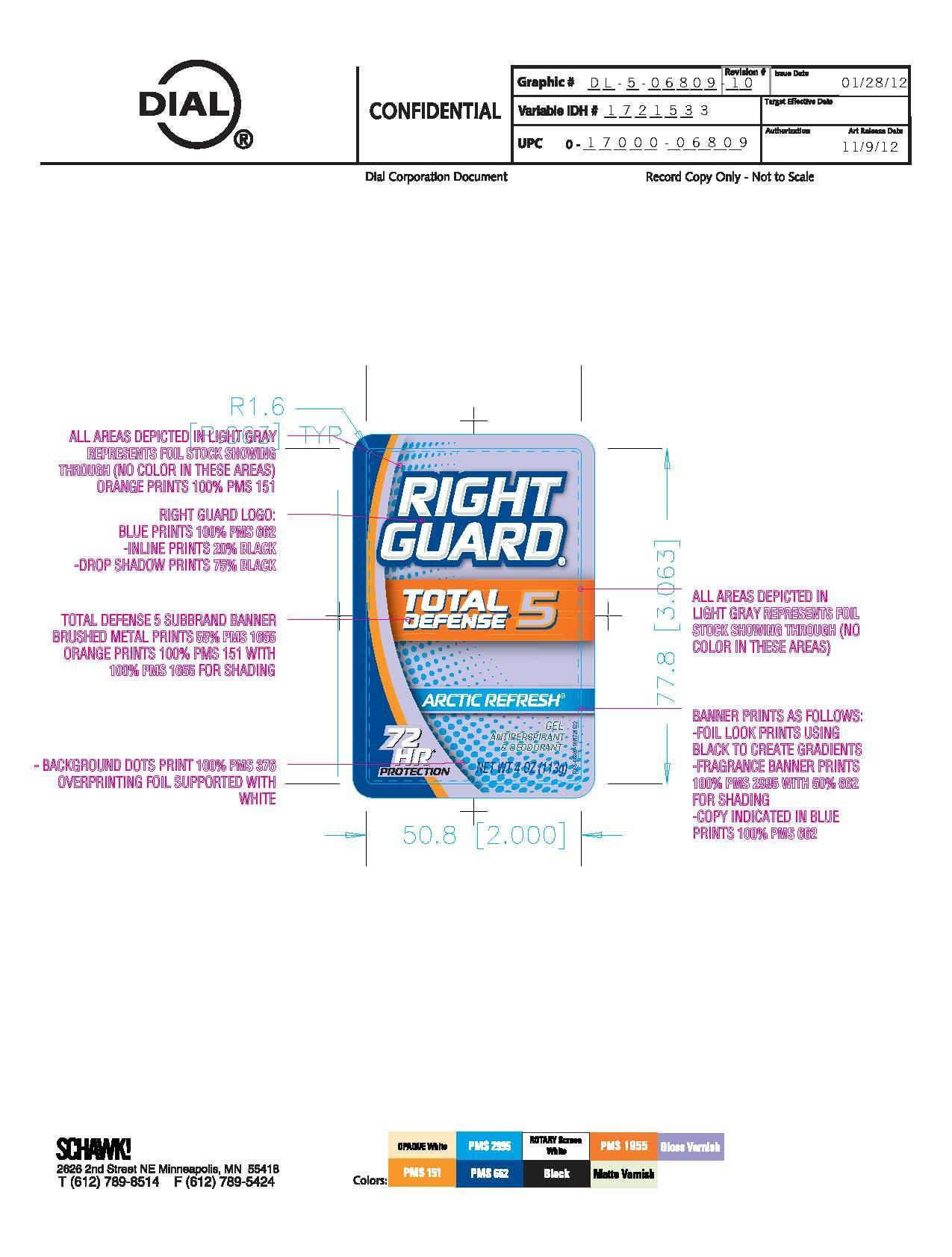 DRUG LABEL: Right Guard Total Defense 5
NDC: 51815-214 | Form: GEL
Manufacturer: VVF Illinois Services LLC
Category: otc | Type: HUMAN OTC DRUG LABEL
Date: 20140220

ACTIVE INGREDIENTS: ALUMINUM ZIRCONIUM OCTACHLOROHYDREX GLY 18.5 g/113 g
INACTIVE INGREDIENTS: WATER; ALCOHOL; CYCLOMETHICONE; PROPYLENE GLYCOL; DIMETHICONE; TRISILOXANE; CALCIUM CHLORIDE; PEG/PPG-18/18 DIMETHICONE; 2-BENZYLHEPTANOL; PHENOXYETHANOL

Right Guard Total Defense 5 Arctic Refresh

Active Ingredient

Aluminum Zirconium Octachlorohydrex GLY 16.4%

Purpose

Antiperspirant

Warnings

For external use only

Do not use on broken skin

Stop use and ask a doctor if rash or irritation occurs

Keep out of reach of children

If swallowed, get medical help or contact poison control center right away

Ask doctor before use if you have kidney disease

USE

Reduces underarm perspiration

Extra effective

Inactive Ingredients

Water, alcohol

denat., cyclomethicone, propylene glycol,

dimethicone, trisiloxane, calcium chloride,

PEG/PPG-18/18 dimethicone, fragrance,

2-benzylhpetanol, phenoxyethanol.

Questions?

1-800-258-DIAL

Directions

Apply to underarms only